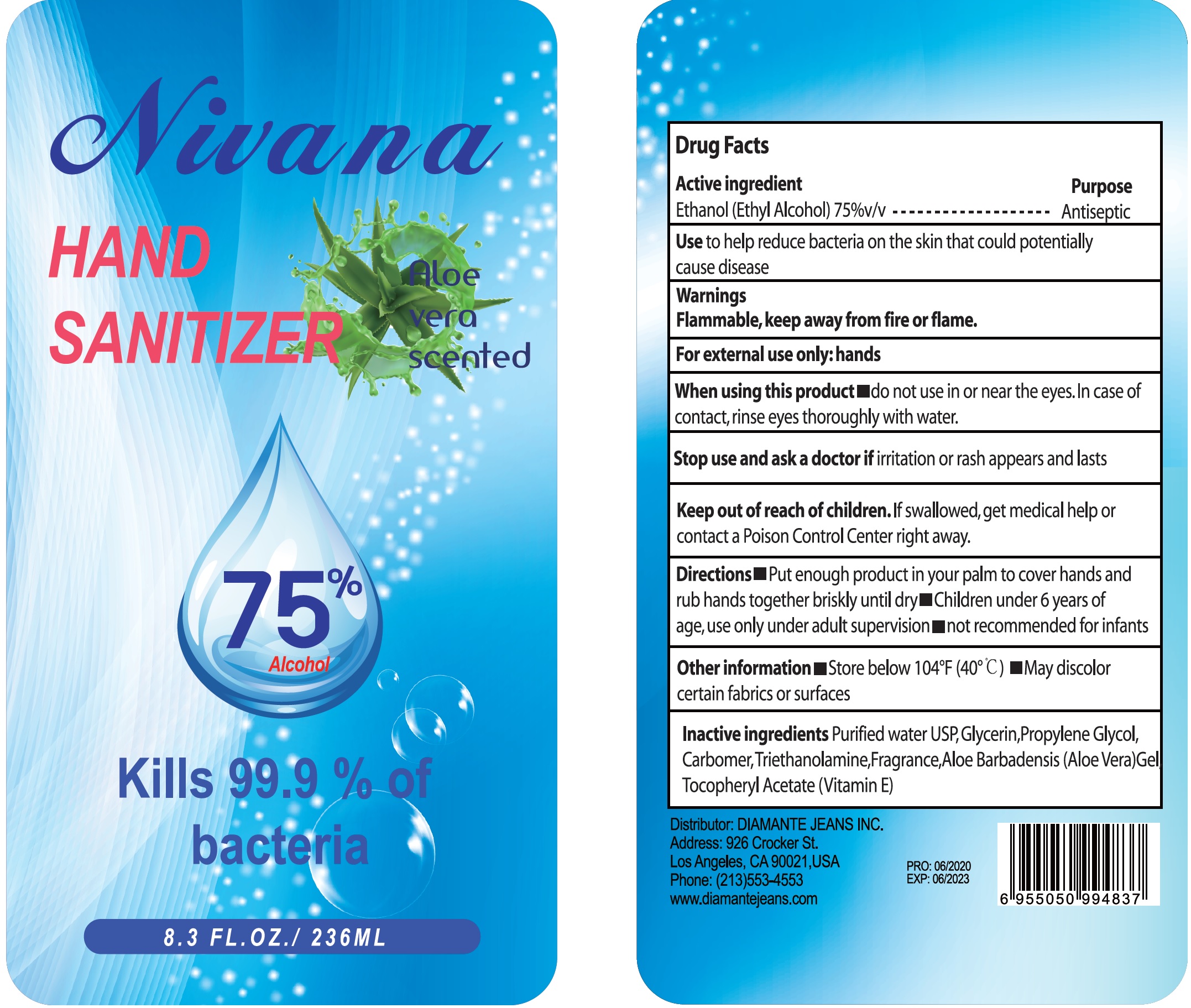 DRUG LABEL: Nivana Hand Sanitizer
NDC: 78554-005 | Form: GEL
Manufacturer: Dinasty Inc.
Category: otc | Type: HUMAN OTC DRUG LABEL
Date: 20201012

ACTIVE INGREDIENTS: ALCOHOL 0.75 mL/1 mL
INACTIVE INGREDIENTS: WATER; GLYCERIN; PROPYLENE GLYCOL; CARBOMER HOMOPOLYMER, UNSPECIFIED TYPE; TROLAMINE; ALOE VERA LEAF; .ALPHA.-TOCOPHEROL

Nivana Hand Sanitizer

Active ingredient

Ethanol (Ethyl Alcohol)75%v/v

Purpose

Antiseptic

Use

to help reduce bacteria on the skin that could potentially cause disease

Warnings

Flammable, keep away from fire or flame.

For external use only:hands

When using this product

- do not use in or near the eyes. In case of contact, rinse eyes thoroughly with water.

Stop use and ask a doctor if

irritation or rash appears and lasts

Keep out of reach of children.

If swallowed, get medical help or contact a Poison Control Center right away.

Directions

- Put enough product in your palm to cover hands and rub hands together briskly until dry.
- Children under 6 years of age, use only under adult supervision
- not recommended for infants

Other information

- Store below 104°F (40°C)
- May discolor certain fabrics or surfaces

Inactive ingredients

Purified water USP, Glycerin, Propylene Glycol, Carbomer, Triethanolamine, Fragrance, Aloe Barbadensis (Aloe Vera) Gel, Tocopheryl Acetate (Vitamin E)